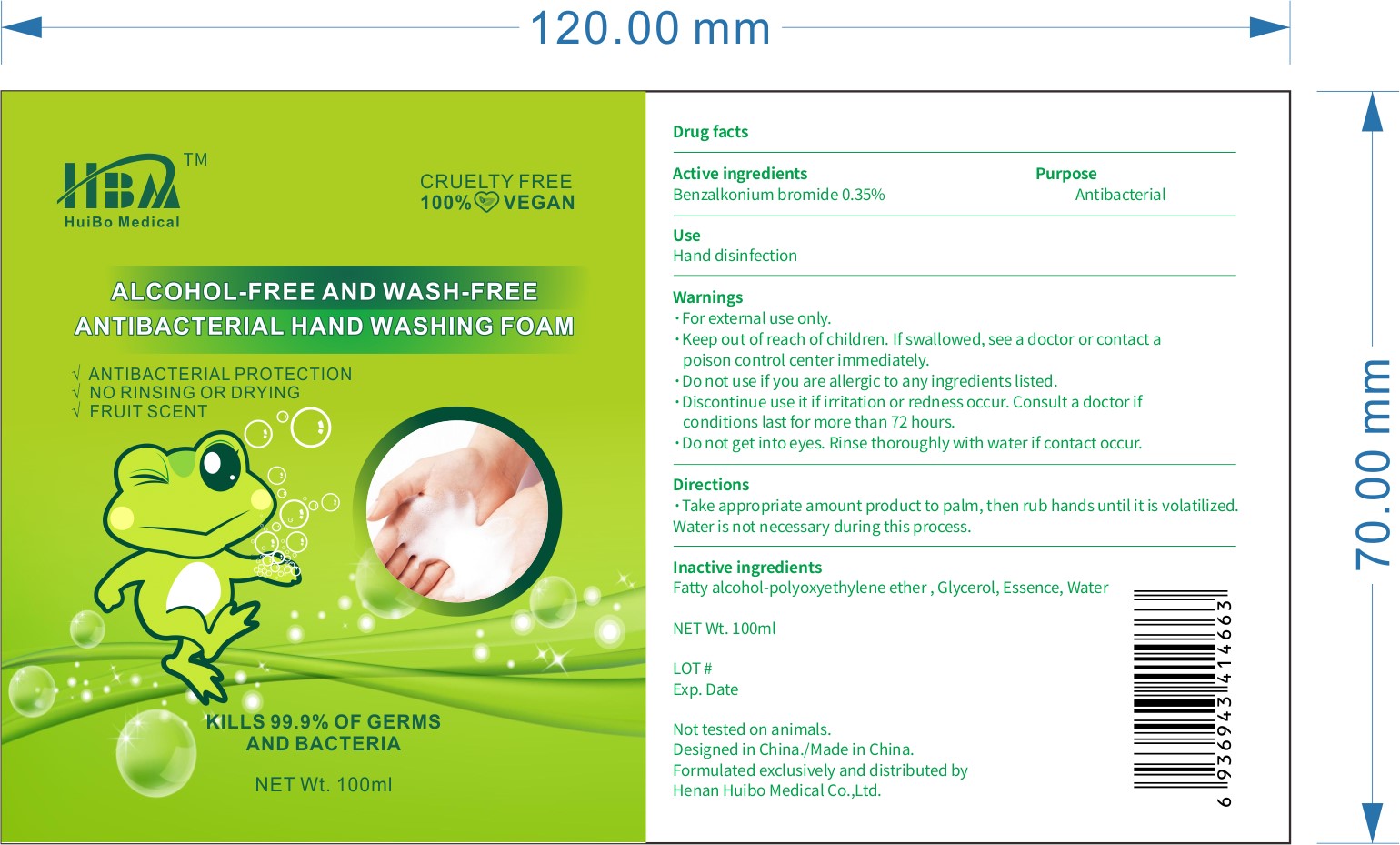 DRUG LABEL: HBA Alcohol Free and Wash Free Antibacterial Hand Washing Foam
NDC: 79158-001 | Form: SOLUTION
Manufacturer: Henan Huibo Medical Co., Ltd.
Category: otc | Type: HUMAN OTC DRUG LABEL
Date: 20200722

ACTIVE INGREDIENTS: BENZALKONIUM BROMIDE 0.35 g/100 mL
INACTIVE INGREDIENTS: GLYCEROL FORMAL; WATER

Benazalkonium Bromide Foam

Active Ingredient

Benzalkonium Bromide 0.35%

Purpose

Antibacterial

Use

■ Hand disinfection

WARNINGS

For external use only

Do not use if you are allergic to any ingredients listed

Discontinue use if irritation or redness occur. Consult a doctor if condition lasts for more than 72 hours

Do not get into eyes. Rinse thoroughly with water if contact occurs

Keep out of reach of children. If swallowed, see a doctor or contact a poison control center immediately

Directions

Take appropriate amount of product to palm, then rub hands untill it is volatilized.

Water is not necesary during this process.

Inactive ingredients

Water, Fatty alcohol-polyoxyethylene ether, Glycerol, Essence, Water